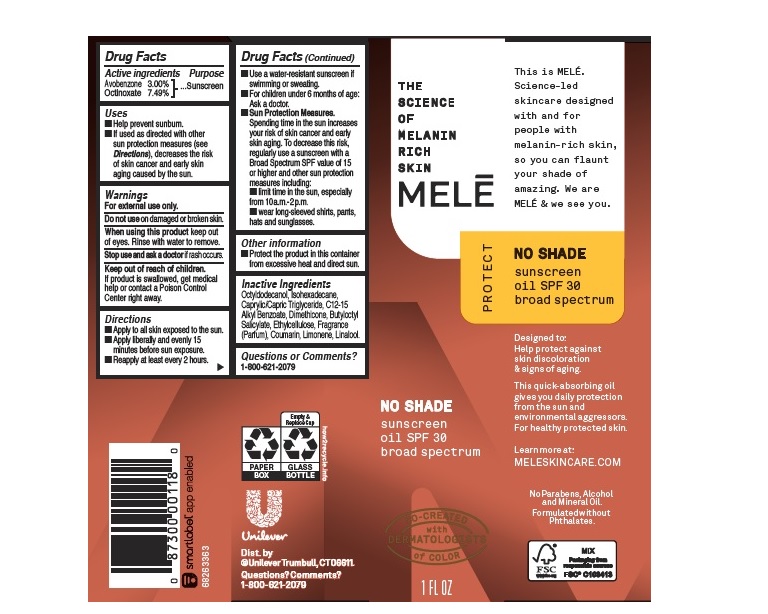 DRUG LABEL: Mele
NDC: 64942-1858 | Form: OIL
Manufacturer: CONOPCO Inc. d/b/a Unilever
Category: otc | Type: HUMAN OTC DRUG LABEL
Date: 20241107

ACTIVE INGREDIENTS: OCTINOXATE 7.49 g/100 mL; AVOBENZONE 2 g/100 mL
INACTIVE INGREDIENTS: OCTYLDODECANOL; ISOHEXADECANE; DIMETHICONE; MEDIUM-CHAIN TRIGLYCERIDES; ALKYL (C12-15) BENZOATE; BUTYLOCTYL SALICYLATE; ETHYLCELLULOSES; COUMARIN; LIMONENE, (+)-; LINALOOL, (+/-)-

Melē No Shade Sunscreen Oil SPF 30

MELĒ NO SHADE SUNSCREEN OIL SPF 30 - (sunscreen, avobenzone, octinoxate) oil

Melē No Shade Sunscreen Oil SPF 30

Drug Facts

Active ingredient
Avobenzone 3%
Octinoxate 7.49%

Purpose

Sunscreen

Uses

Help prevent sunburn
If used as directed with other sun protectionmeaseure (see Directions) decreases the risk of skin cancer and early skin aging caused by the sun

Warnings

For external use only
Do not use on damaged or broken skin
When using this product keep out of eyes. Rinse with water to remove
Stop use and ask a doctor if rash occurs

Keep out of reach of children
If product is swallowed, get medical help or contact a PoisonCcontrol Center right away.

Directions

Apply to all skin exposed to the sun.
Apply liberally and evenly 15 minutes before sun exposure.
Reapply at least every 2 hours.
Use a water resistant sunscreen if swimming or sweating.
For children under 6 months of age. Ask a doctor.
Sun Protection Measures Spending time in the sun increases your risk of skin cancer and early skin aging. To decrease this rish, regularly use a sunscreen with a Broad Spectum SPF value of 15 or higher and other sun protection measures including

limit time in the sun, especiallu from 10a.m. - 2p.m.

wear long-sleeved shirts, pants, hats and sunglasses

Other information

Protect the product in this container from excessive heat and direct sun.

Inactive ingredients

Octyldodecanol, Isohexadecane, Caprylic/Capric Triglyceride, C12-15 Alkyl Benzoate, Dimethicone, Butyloctyl Salicylate, Ethylcellulose, Fragrance (Parfum), Coumarin, Limonene, Linalool.

Questions or Comments?

1-800-621-2079